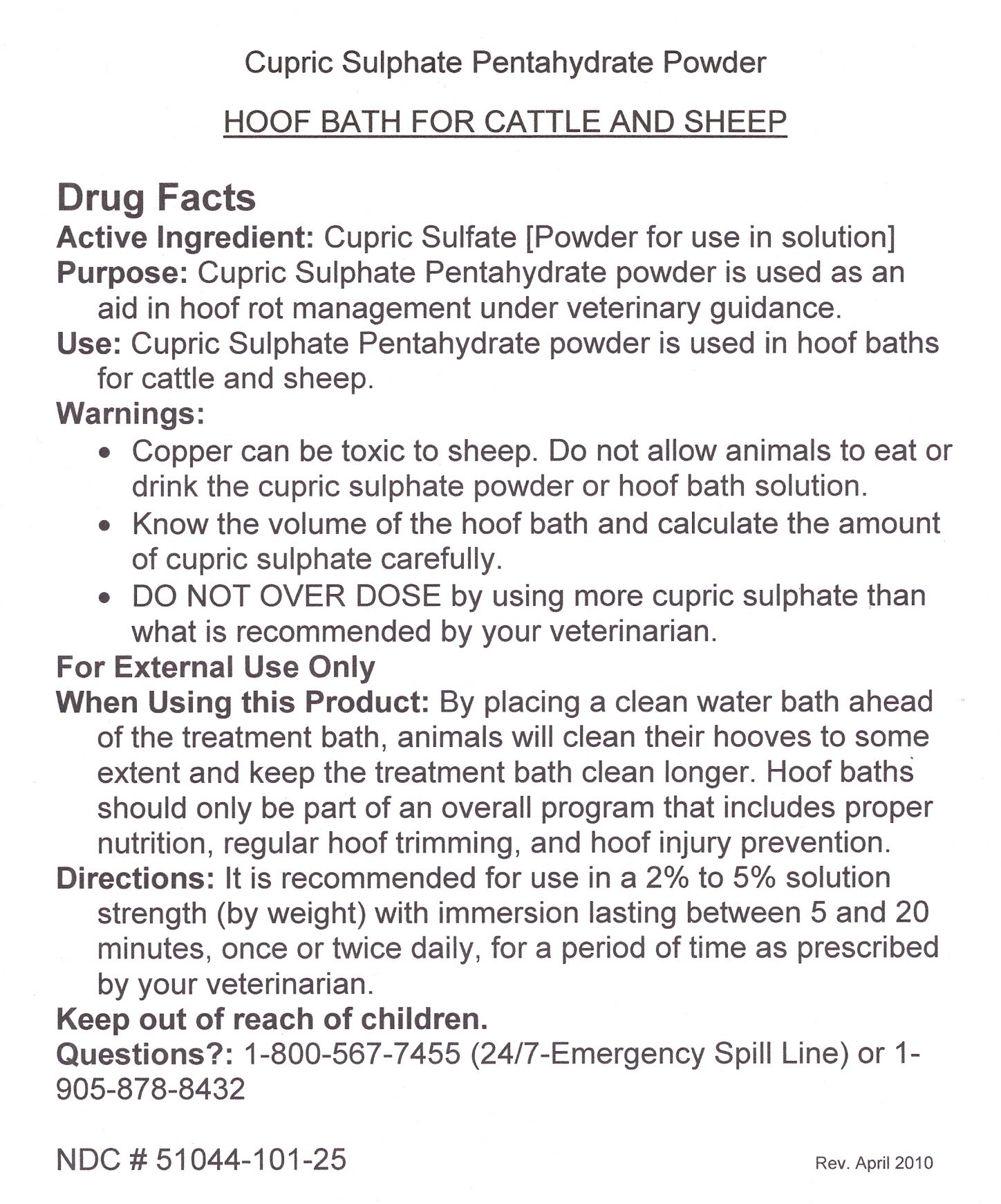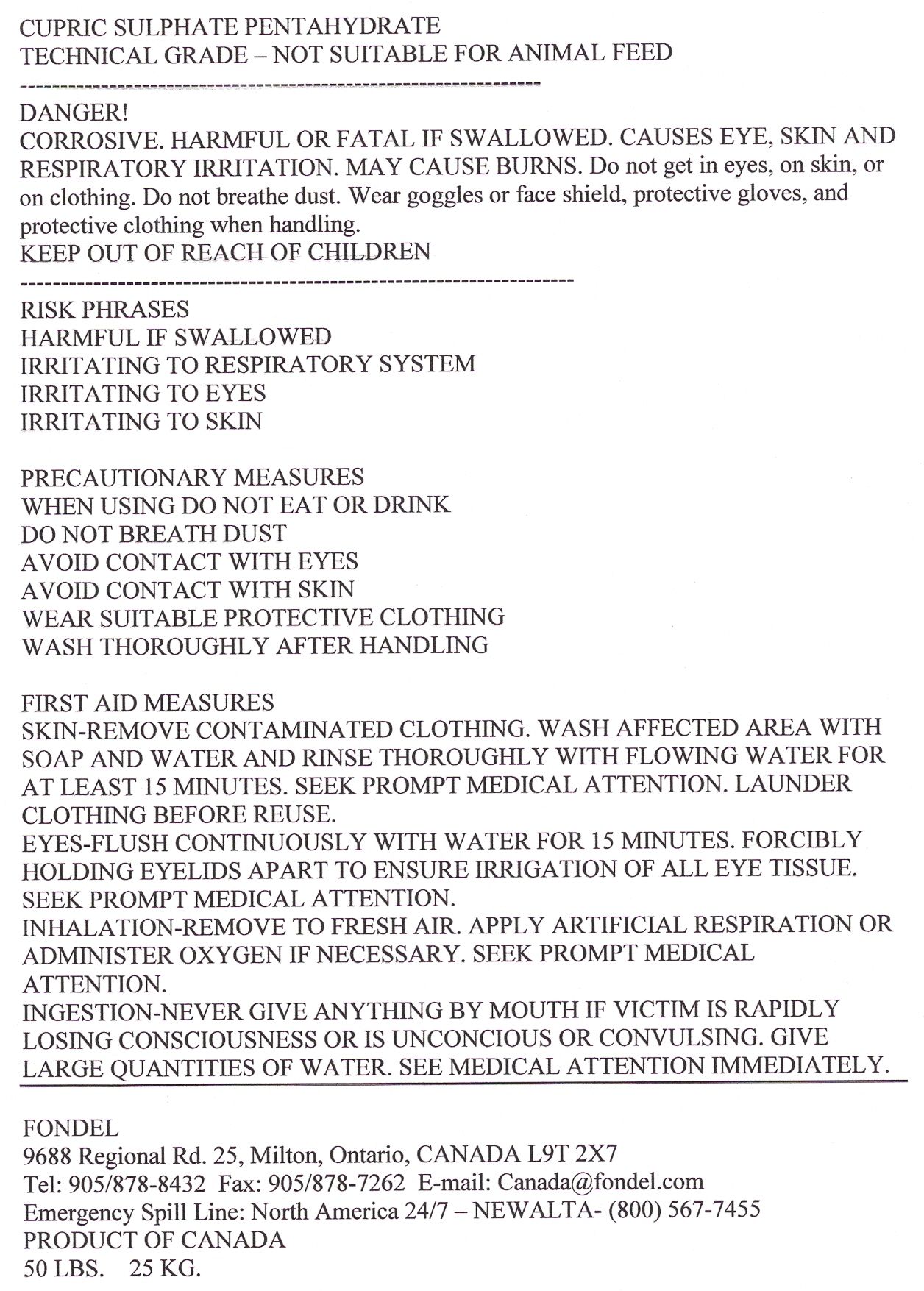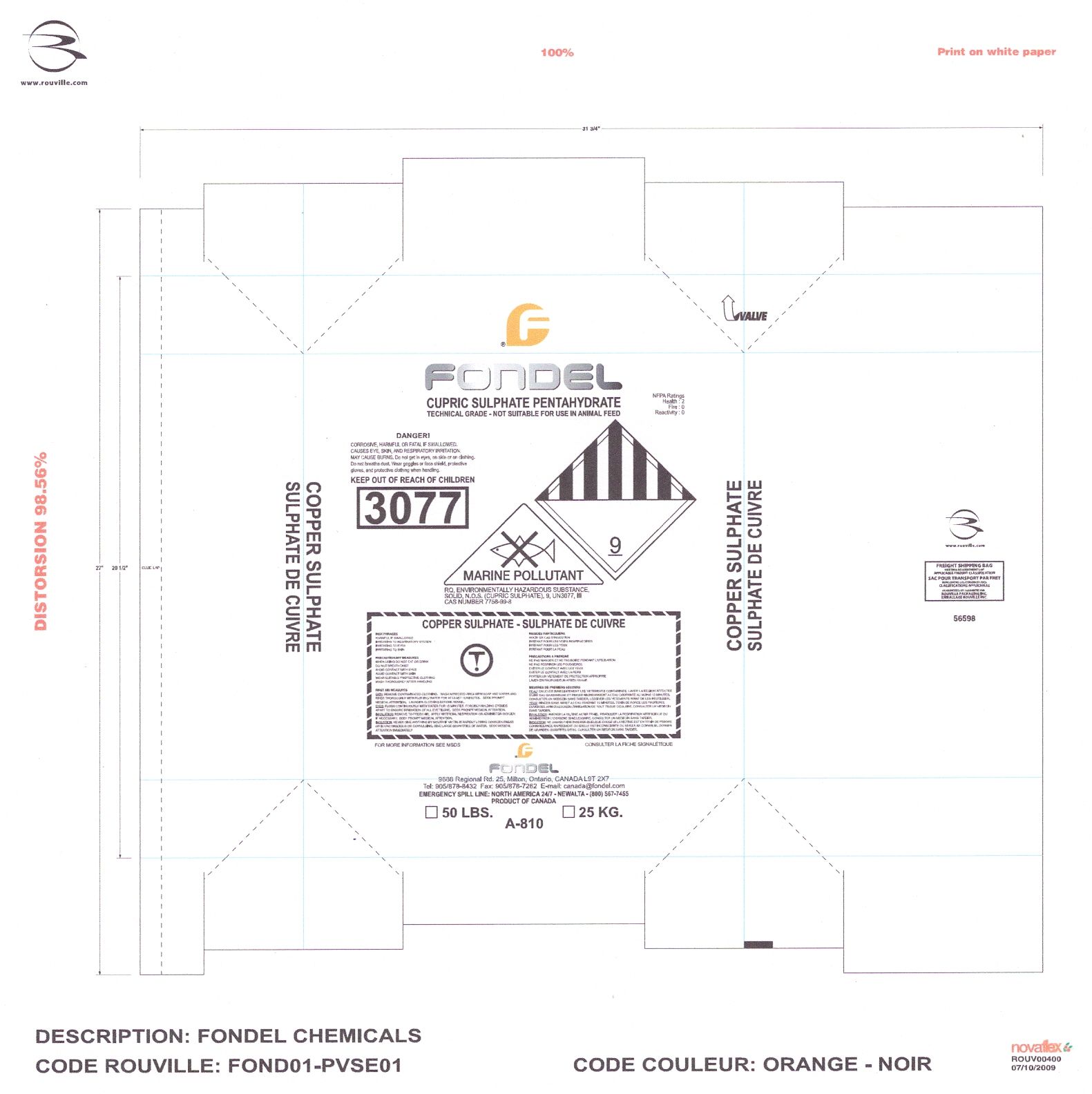 DRUG LABEL: Cupric Sulfate Pentahydrate
NDC: 51044-101 | Form: POWDER, FOR SOLUTION
Manufacturer: Fondel Chemicals Ltd.
Category: animal | Type: OTC ANIMAL DRUG LABEL
Date: 20100625

ACTIVE INGREDIENTS: Cupric Sulfate 0.4 kg/1.6 kg

Cupric Sulfate Pentahydrate Label

Active Ingredient: Cupric Sulfate [Powder for use in solution]

PURPOSE

Purpose: Cupric Sulphate Pentahydrate powder is used as an aid in hoof rot management under veterinary guidance.

Warnings:

- Copper can be toxic to sheep. Do not allow animals to eat or drink the cupric sulphate powder or hoof bath solution.
- Know the volume of the hoof bath and calculate the amount of cupric sulphate carefully.
- Do not overdose by using more cupric sulphate than what is recommended by your veterinarian.

When Using this Product: By placing a clean water bath ahead of the treatment bath, animals will clean their hooves to some extent and keep the treatment bath clean longer. Hoof baths should only be part of an overall program that includes proper nutrition, regular hoof trimming, and hoof injury prevention.

Keep out of reach of children.

QUESTIONS

Questions?: 1-800-567-7455 (24/7-Emergency Spill Line) or 1-905-878-8432